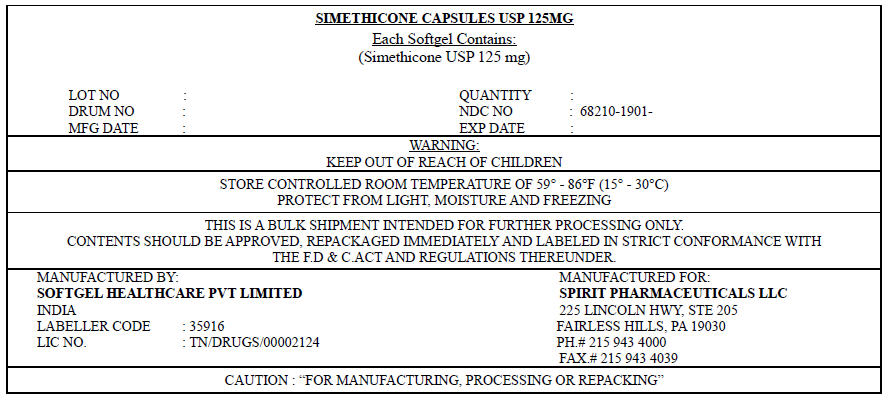 DRUG LABEL: SIMETHICONE
NDC: 68210-1901 | Form: CAPSULE, LIQUID FILLED
Manufacturer: SPIRIT PHARMACEUTICALS,LLC
Category: otc | Type: HUMAN OTC DRUG LABEL
Date: 20100209

ACTIVE INGREDIENTS: DIMETHICONE 125 mg/1 1
INACTIVE INGREDIENTS: GLYCERIN; GELATIN; TITANIUM DIOXIDE; WATER; FD&C RED NO. 3; PEPPERMINT OIL; FD&C BLUE NO. 1

SIMETHICONE, CAPSULES USP 125MG

Drug Facts

Active ingredient (per softgel)

Simethicone 125 mg

Purpose

Antigas

Use

for the relief of

- pressure, bloating, and fullness commonly referred to as gas

Warnings

Keep out of reach of children.

Directions

- adults: swallow with water 1 or 2 softgels as needed after meals and at bedtime
- do not exceed 4 softgels in 24 hours except under the advice and supervision of a physician

Other information

- store at a controlled room temperature 20-25°C (68-77°F)
- protect from light, heat and moisture

Inactive ingredients

D&C yellow 10, FD&C blue 1, FD&C red 40, gelatin, glycerin, hypromellose, peppermint oil, purified water, sorbitol, titanium dioxide

PRINCIPAL DISPLAY PANEL - 125 mg Label

SIMETHICONE CAPSULES USP 125MG

Each Softgel Contains:
(Simethicone USP 125 mg)

LOT NO | : |  |  | QUANTITY | :
DRUM NO | : |  |  | NDC NO | : 68210-1901-
MFG DATE | : |  |  | EXP DATE | :

WARNING:
KEEP OUT OF REACH OF CHILDREN

STORE CONTROLLED ROOM TEMPERATURE OF 59° – 86°F (15° – 30°C)
PROTECT FROM LIGHT, MOISTURE AND FREEZING

THIS IS A BULK SHIPMENT INTENDED FOR FURTHER PROCESSING ONLY.
CONTENTS SHOULD BE APPROVED, REPACKAGED IMMEDIATELY AND LABELED IN STRICT
CONFORMANCE WITH THE F.D&C ACT AND REGULATIONS THEREUNDER.

MANUFACTURED BY:
SOFTGEL HEALTHCARE PVT LIMITED
INDIA
LABELLER CODE : 35916
LIC NO. : TN/DRUGS/00002124

MANUFACTURED FOR:
SPIRIT PHARMACEUTICALS LLC
225 LINCOLN HWY, STE 205
FAIRLESS HILLS, PA 19030
PH.# 215 943 4000
FAX.# 215 943 4039

CAUTION : "FOR MANUFACTURING, PROCESSING OR REPACKING"